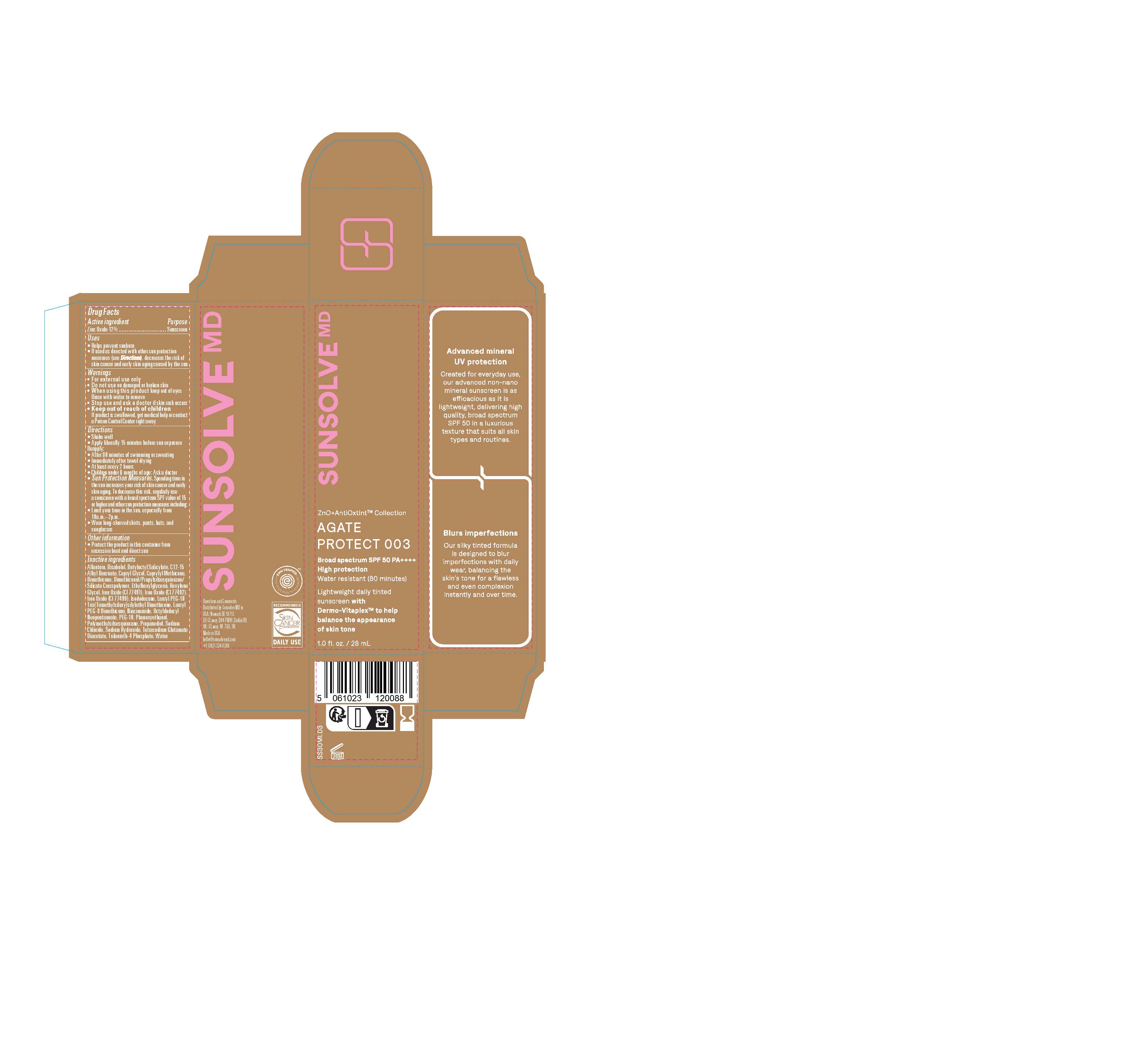 DRUG LABEL: Sunsolve MD Mineral Shade Agate 003
NDC: 84878-403 | Form: LOTION
Manufacturer: Sunsolve MD Inc
Category: otc | Type: HUMAN OTC DRUG LABEL
Date: 20251114

ACTIVE INGREDIENTS: ZINC OXIDE 132 mg/1 mL
INACTIVE INGREDIENTS: FERROSOFERRIC OXIDE; ALLANTOIN; DIMETHICONE; SODIUM CHLORIDE; FERRIC OXIDE YELLOW; CAPRYLYL GLYCOL; FERRIC OXIDE RED; SODIUM HYDROXIDE; WATER; NIACINAMIDE; ETHYLHEXYLGLYCERIN; HEXYLENE GLYCOL; DIMETHICONOL/PROPYLSILSESQUIOXANE/SILICATE CROSSPOLYMER (450000000 MW); PROPANEDIOL; TETRASODIUM GLUTAMATE DIACETATE; PHENOXYETHANOL; .BETA.-TOCOPHEROL; POLYMETHYLSILSESQUIOXANE (4.5 MICRONS); PALMITOYL TETRAPEPTIDE-7; TRILAURETH-4 PHOSPHATE; BUTYLOCTYL SALICYLATE; OCTYLDODECYL NEOPENTANOATE; ISODODECANE; .ALPHA.-BISABOLOL, (+)-; ALKYL (C12-15) BENZOATE; LAURYL PEG-8 DIMETHICONE (300 CPS)

Sunsolve MD Mineral Shade Agate 003